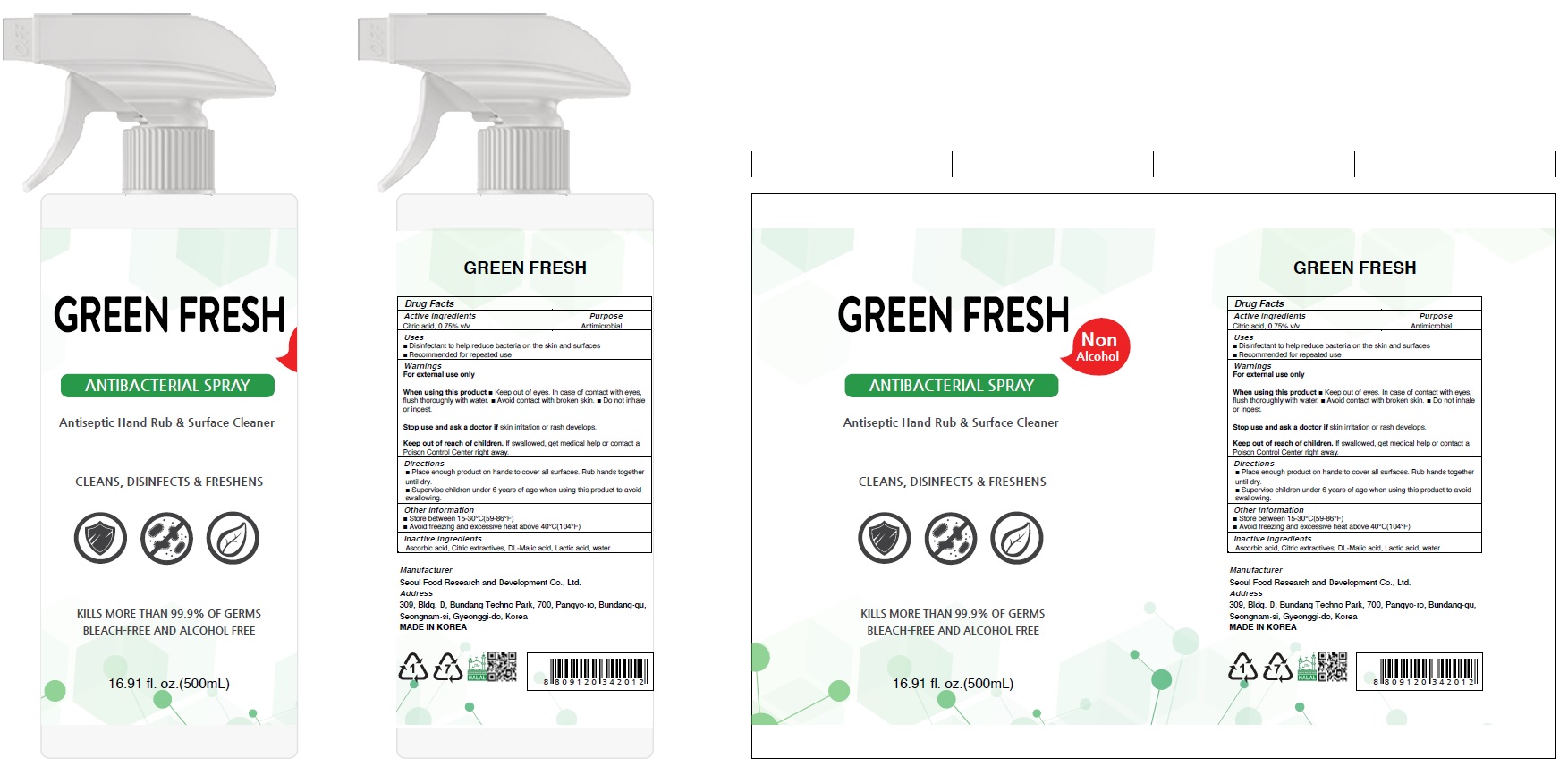 DRUG LABEL: GREEN FRESH
NDC: 80642-040 | Form: SPRAY
Manufacturer: Seoul Food Research & Development Co., Ltd.
Category: otc | Type: HUMAN OTC DRUG LABEL
Date: 20201023

ACTIVE INGREDIENTS: CITRIC ACID MONOHYDRATE 3.75 g/500 mL
INACTIVE INGREDIENTS: Ascorbic acid; MALIC ACID; Lactic acid; Water

ACTIVE INGREDIENT

Citiric acid 0.75% v/v

INACTIVE INGREDIENTS

Ascorbic acid, Citric extractives, DL-Malic acid, Lactic acid, Water

PURPOSE

Antimicrobial

WARNINGS

For external use only

When using this product ■ Keep out of eyes. In case of contact with eyes, flush thoroughly with water. ■ Avoid contact with broken skin. ■ Do not inhale or ingest.

Stop use and ask a doctor if skin irritation or rash develops.

Keep out of reach of children. If swallowed, get medical help or contact a Poison Control Center right away.

Keep out of reach of children. If swallowed, get medical help or contact a Poison Control Center right away.

Uses

■ Disinfectant to help reduce bacteria on the skin and surfaces
■ Recommended for repeated use

Directions

■ Place enough product on hands to cover all surfaces. Rub hands together until dry.
■ Supervise children under 6 years of age when using this product to avoid swallowing.

Other information

■ Store between 15-30℃(59-86℉)
■ Avoid freezing and excessive heat above 40℃(104℉)